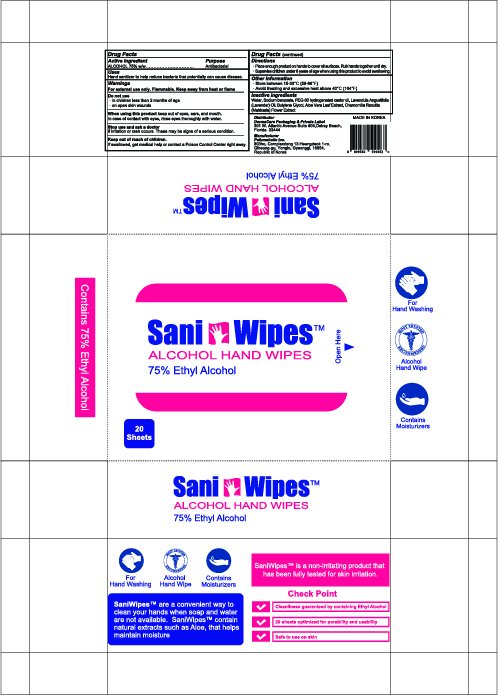 DRUG LABEL: SANI WIPES
NDC: 75773-275 | Form: CLOTH
Manufacturer: Perfumeholic Inc
Category: otc | Type: HUMAN OTC DRUG LABEL
Date: 20200928

ACTIVE INGREDIENTS: ALCOHOL 0.75 1/1 1
INACTIVE INGREDIENTS: BUTYLENE GLYCOL; WATER; ALOE VERA LEAF; CHAMOMILE; PEG-60 HYDROGENATED CASTOR OIL; LAVENDER OIL; SODIUM BENZOATE

Perfumeholic Inc | SANI WIPES | 75773-275-20 | 20 Sheets